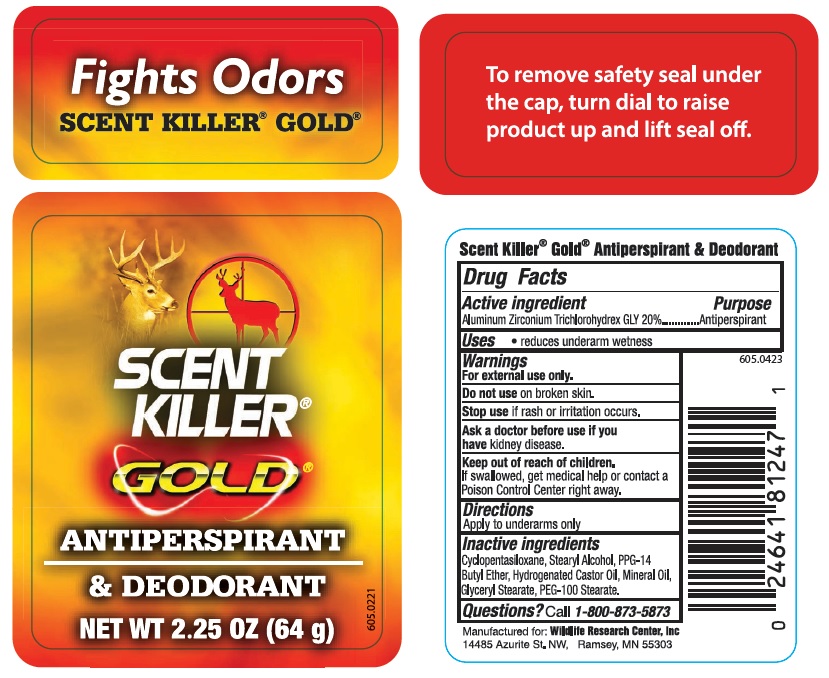 DRUG LABEL: Scent Killer Gold
NDC: 10889-416 | Form: STICK
Manufacturer: VVF Kansas Services LLC
Category: otc | Type: HUMAN OTC DRUG LABEL
Date: 20171222

ACTIVE INGREDIENTS: ALUMINUM ZIRCONIUM TRICHLOROHYDREX GLY 12.8 g/64 g
INACTIVE INGREDIENTS: GLYCERYL STEARATE SE; PEG-100 STEARATE; PPG-14 BUTYL ETHER; MINERAL OIL; HYDROGENATED CASTOR OIL; CYCLOMETHICONE 5; STEARYL ALCOHOL

Scent Killer Gold Antiperspirant & Deodorant

Active Ingredient

Aluminum Zirconium Trichlorohydrex GLY 20%

Purpose

Antiperspirant

Uses

- reduces underarm wetness

Warnings

For external use only.

Do not use on broken skin.

Stop use if rash or irritation occurs.

Ask a doctor before use if you have kidney disease.

Keep out of reach of children.

If swallowed, get medical help or contact a

Poison Control Center right away.

Directions

Apply to underarms only

Inactive ingredients

Cyclopentasiloxane, Stearyl Alcohol, PPG-14

Butyl Ether, Hydrogenated Castor Oil, Mineral Oil,

Glyceryl Stearate, PEG-100 Stearate.

Questions?

Call 1-800-873-5873

Scent Killer ® Gold ® Antiperspirant & Deodorant

Manufactured for: Wildlife Research Center, Inc

14485 Azurite St. NW

Ramsey, MN 55303

Back Cap Label:

To remove safety seal under the cap, turn dial to raise product up and lift seal off.

Scent Killer ® Gold ® Antiperspirant & Deodorant

NET WT 2.25 OZ (64 g)

Front Cap Label:

Fights Odors

Scent Killer ® Gold ®